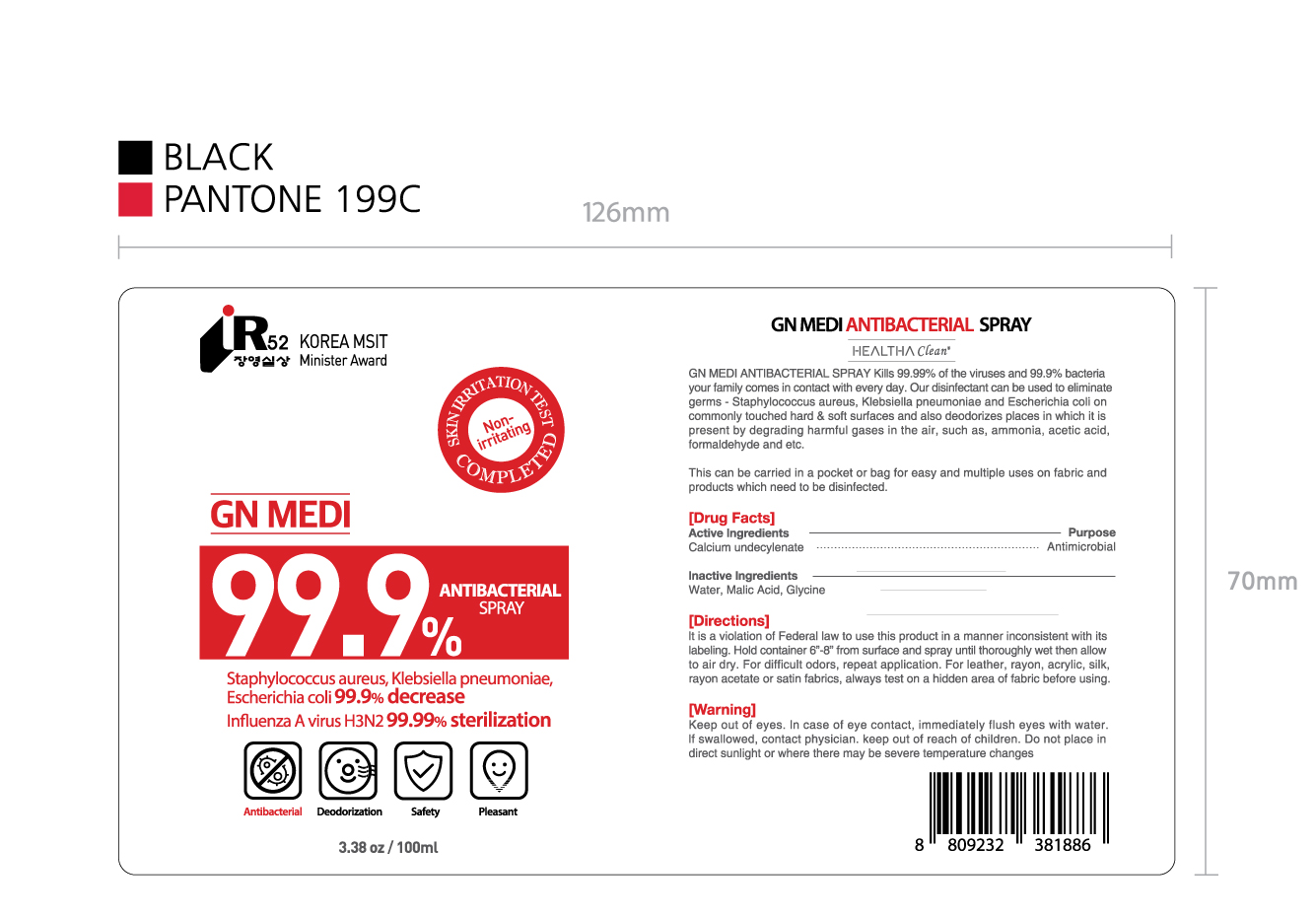 DRUG LABEL: GN MEDI ANTIBACTERIALSPRAY
NDC: 79797-301 | Form: LIQUID
Manufacturer: GNCOS CO., LTD.
Category: otc | Type: HUMAN OTC DRUG LABEL
Date: 20200730

ACTIVE INGREDIENTS: CALCIUM UNDECYLENATE 1 g/100 g
INACTIVE INGREDIENTS: MALIC ACID 0.2 g/100 g; ZINC OXIDE 0.8 g/100 g; GLYCINE 0.2 g/100 g; WATER 97.8 g/100 g

Active ingredients

Calcium undecylenate

Purpose

Antimicrobial

Inactive Ingredients

water, malic acid,Glycine

Directions

it is a violation of Federal law to use this product in a manner inconsistent with its labeling.

hold container 6"-8" from surface and hands spray until thoroughly wet then allow to air dry.

our disinfectant can be used to eliminate germs- on commonly touched hard & soft surfaces and also deodorizes places in which it is present by degrading harmful gases in the air.

Do not use

in children less than 2 months of age.

on open skin wounds

when using

our disinfectant can be used to eliminate germs- on commonly touched hard & soft surfaces and also deodorizes places in which it is present by degrading harmful gases in the air.

Stop use and ask a doctor

in case of eye contact, immediately flush eyes with water. if swallowed, contact physician.

WARNINGS

do not place in direct sunlight or where there may be serve temperature changes.

keep out of rech of children

use

heltha clean disintectant spray kills of the viruses and bacteria your family comes in contact with every day.

For leather, rayon, acrylic, silk, rayon acetate or satin fabrics, always test on a hidden area of fabric before using.

Other information

This can be carried in a pocket or bag for easy and multiple uses on fabric and products which need to be disinfected.

Package Label

79797-301-01